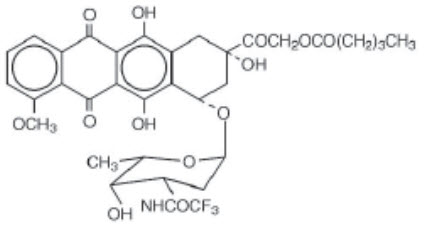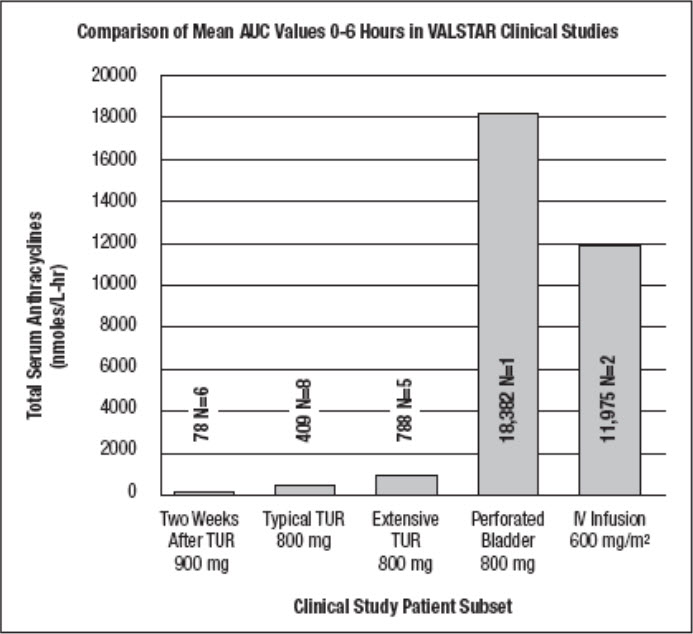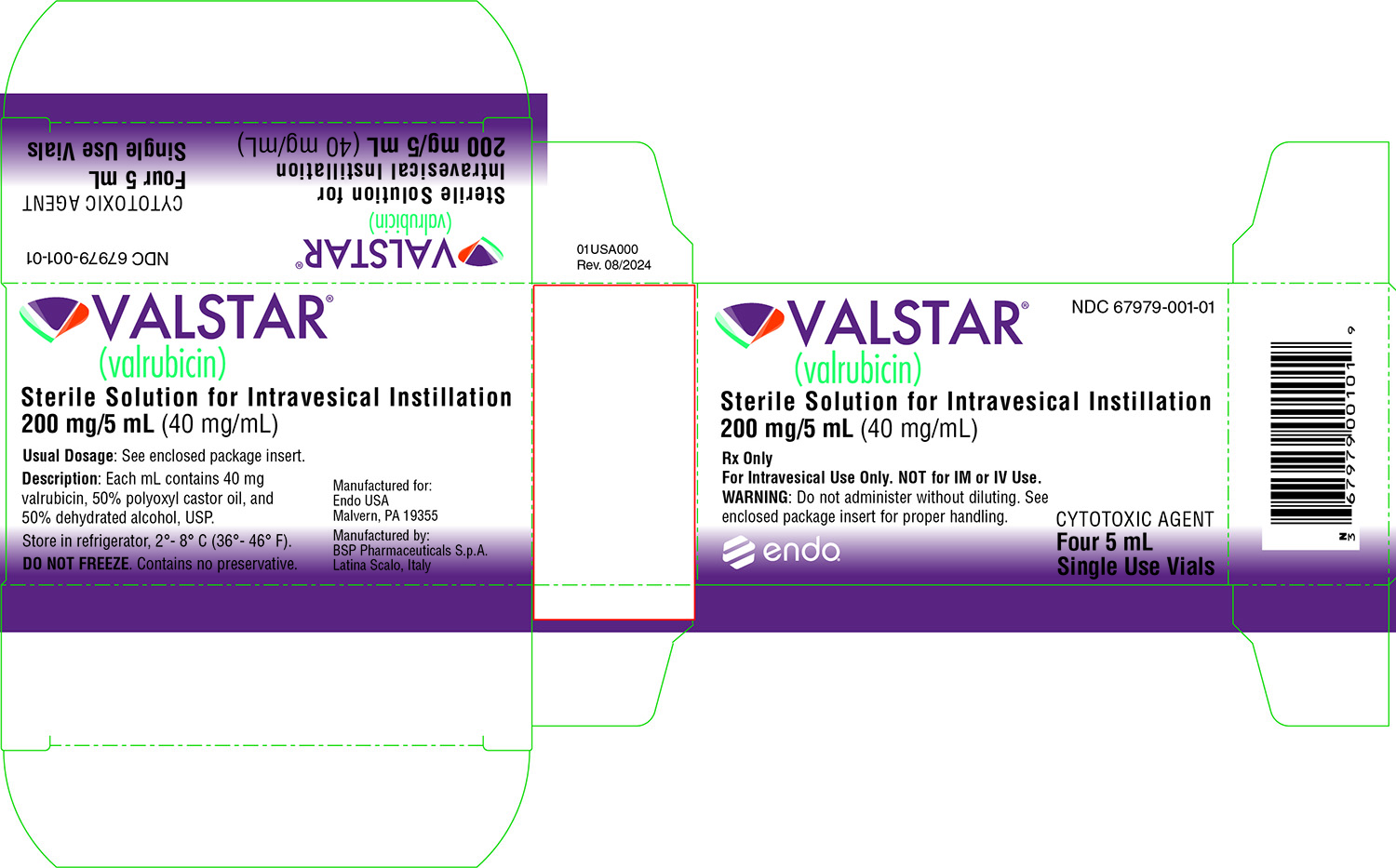 DRUG LABEL: Valstar
NDC: 67979-001 | Form: SOLUTION, CONCENTRATE
Manufacturer: Endo USA, Inc.
Category: prescription | Type: HUMAN PRESCRIPTION DRUG LABEL
Date: 20241031

ACTIVE INGREDIENTS: VALRUBICIN 40 mg/1 mL
INACTIVE INGREDIENTS: ALCOHOL; POLYOXYL 35 CASTOR OIL; NITROGEN

HIGHLIGHTS OF PRESCRIBING INFORMATION

These highlights do not include all the information needed to use VALSTAR safely and effectively. See full prescribing information for VALSTAR.
VALSTAR®(valrubicin) solution, for intravesical use
Initial U.S. Approval: 1981

1 INDICATIONS AND USAGE

- VALSTAR is an anthracycline topoisomerase inhibitor indicated for intravesical therapy of BCG-refractory carcinoma in situ(CIS) of the urinary bladder in patients for whom immediate cystectomy would be associated with unacceptable morbidity or mortality. (1)

2 DOSAGE AND ADMINISTRATION

- For Intravesical Use Only. (2.1)
- VALSTAR is recommended at a dose of 800 mg administered intravesically once a week for six weeks. (2.1)
- Delay administration at least two weeks after transurethral resection and/or fulguration. (2.1)
- Warm VALSTAR slowly to room temperature, but do not heat. (2.1)
- Use caution when handling and preparing the solution of VALSTAR. (2.2)

3 DOSAGE FORMS AND STRENGTHS

- Injection: 200 mg/5 mL in single-use vials (3)

4 CONTRAINDICATIONS

- Perforated bladder or compromised bladder mucosa (4, 5.2)
- Hypersensitivity to anthracyclines or polyoxyl castor oil. (4)
- Concurrent urinary tract infections. (4)
- Patients with a small bladder capacity unable to tolerate a 75 mL instillation. (4)

5 WARNINGS AND PRECAUTIONS

- Delaying cystectomy can lead to development of metastatic bladder cancer, which is lethal. (5.1)
- Do not administer VALSTAR to patients with a perforated bladder or to those in whom the integrity of the bladder mucosa has been compromised. (5.2, 12.3)
- Evaluate the status of the bladder before the intravesical instillation of VALSTAR. (5.3)
- Use with caution in patients with severe irritable bladder symptoms. (5.4)
- Embryo-Fetal Toxicity: VALSTAR can cause fetal harm. Advise females of reproductive potential of the potential risk to a fetus and to use effective contraception. (5.5, 8.1, 8.3)

6 ADVERSE REACTIONS

The most frequently reported adverse reactions (>5%) after administration of VALSTAR are urinary frequency, dysuria, urinary urgency, bladder spasm, hematuria, bladder pain, urinary incontinence, cystitis, urinary tract infection, nocturia, local burning symptoms, abdominal pain, and nausea. (6.1)

To report SUSPECTED ADVERSE REACTIONS, contact Endo at 1-800-462-3636 or FDA at 1-800-FDA-1088 orwww.fda.gov/medwatch.

8 USE IN SPECIFIC POPULATIONS

- Lactation: Advise not to breastfeed. (8.2)

FULL PRESCRIBING INFORMATION

1 INDICATIONS AND USAGE

VALSTAR is an anthracycline topoisomerase inhibitor indicated for intravesical therapy of BCG-refractory carcinoma in situ(CIS) of the urinary bladder in patients for whom immediate cystectomy would be associated with unacceptable morbidity or mortality.

2 DOSAGE AND ADMINISTRATION

2.1 Recommended Dosing

For Intravesical Use Only. Do NOT administer by intravenous or intramuscular routes.

VALSTAR is recommended at a dose of 800 mg administered intravesically once a week for six weeks. Delay administration at least two weeks after transurethral resection and/or fulguration [ see Warnings and Precautions (5.2, 5.3)].

2.2 Preparation, Handling, and Administration

Handle and dispose of VALSTAR in a manner consistent with other cytotoxic drugs.^1The use of goggles, gloves, and protective gowns is recommended during preparation and administration of the drug.

VALSTAR contains polyoxyl castor oil, which has been known to cause leaching of di(2-ethylhexyl) phthalate (DEHP) a hepatotoxic plasticizer, from polyvinyl chloride (PVC) bags and intravenous tubing. VALSTAR should be prepared and stored in glass, polypropylene, or polyolefin containers and tubing. It is recommended that non-DEHP containing administration sets, such as those that are polyethylene-lined, be used.

VALSTAR is a sterile, clear red solution. Visually inspect for particulate matter and discoloration prior to administration. At temperatures below 4°C (39°F), polyoxyl castor oil may begin to form a waxy precipitate. If this happens, the vial should be warmed in the hand until the solution is clear. If particulate matter is still seen, do not administer VALSTAR.

For each instillation, slowly allow four 5 mL vials (200 mg valrubicin/5 mL vial) to warm to room temperature, but do not heat. Withdraw 20 mL of VALSTAR from the four vials and dilute with 55 mL of 0.9% Sodium Chloride Injection, USP to provide 75 mL of a diluted VALSTAR solution. VALSTAR diluted in 0.9% Sodium Chloride Injection, USP for administration is stable for 12 hours at temperatures up to 25°C (77°F). Since compatibility data are not available, do not mix VALSTAR with other drugs.

Insert a urethral catheter into the patient's bladder under aseptic conditions, drain the bladder, and instill the diluted 75 mL VALSTAR solution slowly via gravity flow over a period of several minutes. Withdraw the catheter and retain VALSTAR in the bladder for two hours before voiding. At the end of two hours, all patients should void. Some patients may be unable to retain the drug for the full two hours. Instruct patients to maintain adequate hydration following VALSTAR treatment [see Patient Counseling Information (17)] .

3 DOSAGE FORMS AND STRENGTHS

200 mg/5 mL sterile, clear red, solution in single-use vials for intravesical instillation upon dilution.

4 CONTRAINDICATIONS

VALSTAR is contraindicated in patients with:

- Perforated bladder [ see Warnings and Precautions (5.2)]
- Known hypersensitivity to anthracyclines or polyoxyl castor oil
- Active urinary tract infection
- Small bladder capacity and unable to tolerate a 75 mL instillation

5 WARNINGS AND PRECAUTIONS

5.1 Risk of Metastatic Bladder Cancer with Delayed Cystectomy

Inform patients that VALSTAR has been shown to induce complete response in only about 1 in 5 patients with BCG-refractory CIS, and that delaying cystectomy could lead to development of metastatic bladder cancer, which is lethal. The exact risk of developing metastatic bladder cancer from such a delay may be difficult to assess [see Clinical Studies (14)] but increases the longer cystectomy is delayed in the presence of persisting CIS. If there is not a complete response of CIS to treatment after 3 months or if CIS recurs, reconsider cystectomy.

5.2 Risk in Patients with Perforated Bladder

Evaluate the bladder before the intravesical instillation of drug and do not administer VALSTAR to patients with a perforated bladder or to those in whom the integrity of the bladder mucosa has been compromised [see Contraindications (4)] . In case of bladder perforation, delay the administration of VALSTAR until bladder integrity has been restored. One patient with a perforated bladder who received 800 mg of VALSTAR intravesically developed severe leukopenia and neutropenia approximately two weeks after drug administration [see Clinical Pharmacology (12.3)] .

5.3 Risk in Patients Undergoing Transurethral Resection of the Bladder (TURB)

To avoid systemic exposure to VALSTAR for the patients undergoing TURB, evaluate the status of the bladder before the intravesical instillation of drug. Delay administration at least two weeks after transurethral resection and/or fulguration.

5.4 Risk in Patients with Irritable Bladder Symptoms

Use VALSTAR with caution in patients with severe irritable bladder symptoms. Bladder spasm and spontaneous discharge of the intravesical instillate may occur; clamping of the urinary catheter is not advised.

5.5 Embryo-Fetal Toxicity

Based on findings in animal studies and its mechanism of action, VALSTAR can cause fetal harm when administered to a pregnant woman [see Clinical Pharmacology (12.1and 12.3)] . In animal reproduction studies, intravenous administration of valrubicin to pregnant rats during the period of organogenesis at a dose about 0.2 times the recommended human intravesical dose caused embryo-fetal malformations and increased resorptions. Advise females who might become pregnant of the potential risk to a fetus.

Advise females of reproductive potential to use effective contraception during treatment with VALSTAR and for 6 months following the final dose [see Use in Specific Populations (8.1and 8.3)] .

6 ADVERSE REACTIONS

6.1 Clinical Trial Experience

Because clinical trials are conducted under widely varying conditions, adverse reaction rates observed in the clinical trials of a drug cannot be directly compared to rates in the clinical trials of another drug and may not reflect the rates observed in practice.

The safety of VALSTAR was assessed in 230 patients with transitional cell carcinoma of the bladder, including 205 patients who received multiple weekly doses. One hundred seventy-nine of the 205 patients received the approved dose and schedule of 800 mg weekly for multiple weeks.

Approximately 84% of patients who received intravesical VALSTAR in clinical studies experienced local adverse reactions. The local adverse reactions associated with VALSTAR usually occur during or shortly after instillation and resolve within 1 to 7 days after the instillate is removed from the bladder. Seven out of 143 patients (5%) who were scheduled to receive six doses of VALSTAR failed to receive all of the planned doses because of the occurrence of local bladder symptoms.

TABLE 1 displays the frequency of the local adverse reactions at baseline and during treatment among 179 patients who received 800 mg doses of VALSTAR in a multiple-cycle treatment regimen.

TABLE 1 Local Adverse Reactions Before and During Treatment with VALSTAR (N=179)
Adverse Reaction | Before Treatment | During 6-week; Course of Treatment
ANY LOCAL; BLADDER SYMPTOM | 45% | 88%
Urinary Frequency | 30% | 61%
Dysuria | 11% | 56%
Urinary Urgency | 27% | 57%
Bladder Spasm | 3% | 31%
Hematuria | 11% | 29%
Bladder Pain | 6% | 28%
Urinary Incontinence | 7% | 22%
Cystitis | 4% | 15%
Nocturia | 2% | 7%
Local Burning Symptoms –; Procedure Related | 0% | 5%
Urethral Pain | 0% | 3%
Pelvic Pain | 1% | 1%
Hematuria (Gross) | 0% | 1%

TABLE 2 displays the adverse reactions other than local bladder symptoms that occurred in 1% or more of the 230 patients who received at least one dose of VALSTAR in a clinical trial.

TABLE 2 Systemic Adverse Reactions (≥ 1%) Following Intravesical Administration of VALSTAR (N=230)
Body System; Preferred Term
Body as a Whole
Abdominal Pain | 5%
Asthenia | 4%
Headache | 4%
Malaise | 4%
Back Pain | 3%
Chest Pain | 3%
Fever | 2%
Cardiovascular
Vasodilation | 2%
Digestive
Nausea | 5%
Diarrhea | 3%
Vomiting | 2%
Flatulence | 1%
Hemic and Lymphatic
Anemia | 2%
Metabolic and Nutritional
Hyperglycemia | 1%
Peripheral Edema | 1%
Musculoskeletal
Myalgia | 1%
Nervous
Dizziness | 3%
Respiratory
Pneumonia | 1%
Skin and Appendages
Rash | 3%
Urogenital
Urinary Tract Infection | 15%
Urinary Retention | 4%
Hematuria (miscroscopic) | 3%

Adverse reactions other than local reactions that occurred in less than 1% of the patients who received VALSTAR intravesically in clinical trials are listed below.

Digestive System:Tenesmus
Metabolic and Nutritional:Nonprotein nitrogen increased
Skin and Appendages:Pruritus
Special Senses:Taste loss
Urogenital System:Local skin irritation, poor urine flow, and urethritis

7 DRUG INTERACTIONS

No drug interaction studies were conducted.

8 USE IN SPECIFIC POPULATIONS

8.1 Pregnancy

Risk Summary

Based on findings in animal studies and its mechanism of action, VALSTAR can cause fetal harm when administered to a pregnant females [see Clinical Pharmacology (12.1and 12.3)] . There are no available data in pregnant females to inform the drug-associated risk. In animal reproduction studies, intravenous administration of valrubicin to pregnant rats during the period of organogenesis at a dose about 0.2 times the recommended human intravesical dose caused embryo-fetal malformations and increased resorptions [see Data]. Advise females who are or might become pregnant of the potential risk to a fetus.

In the U.S. general population, the estimated background risk of major birth defects and miscarriage in clinically-recognized pregnancies is 2% to 4% and 15% to 20%, respectively.

Data

Animal Data

Daily intravenous administration of valrubicin to pregnant rats during the period of organogenesis at doses ≥ 12 mg/kg (about 0.2 times the recommended human intravesical dose on a mg/m^2basis) was embryo-fetal toxic and teratogenic. Administration of 12 mg/kg resulted in fetal malformations. A dose of 24 mg/kg (about 0.3 times the recommended human intravesical dose on a mg/m^2basis) caused numerous, severe alterations in the skull and skeleton of the developing fetuses. This dose also caused an increase in fetal resorptions and a decrease in viable fetuses.

8.2 Lactation

Risk Summary

There are no data on the presence of valrubicin or its metabolites in human milk, the effects of valrubicin on the breast-fed infant, or its effects on milk production. Because of the potential for serious adverse reactions in breast-fed infants from valrubicin, advise a lactating female not to breastfeed during treatment with VALSTAR and for 2 weeks after the final dose.

8.3 Females and Males of Reproductive Potential

Contraception

Females

VALSTAR can cause fetal harm when administered to a pregnant female. Advise females of reproductive potential to use effective contraception during treatment with VALSTAR and for 6 months after the final dose [see Use in Specific Populations (8.1)] .

Males

Based on genotoxicity findings, advise men with female partners of reproductive potential to use effective contraception during treatment with VALSTAR and for 3 months following the final dose [see Non Clinical Toxicology (13.1)]

Infertility

Males

Studies of the effects of VALSTAR on human male or female fertility have not been done. Based on findings in animal studies, VALSTAR may impair fertility in males of reproductive potential [see Nonclinical Toxicology (13.1)] .

8.4 Pediatric Use

Safety and effectiveness in pediatric patients have not been established.

8.5 Geriatric Use

Because carcinoma in situof the bladder generally occurs in older individuals, 85% of the patients enrolled in the clinical studies of VALSTAR were more than 60 years of age (49% of the patients were more than 70 years of age). In the primary efficacy studies, the mean age of the population was 69.5 years. There are no specific precautions regarding use of VALSTAR in geriatric patients who are otherwise in good health.

10 OVERDOSAGE

There is no known antidote for overdoses of VALSTAR. The primary anticipated complications of overdosage associated with intravesical administration would be consistent with irritable bladder symptoms.

Myelosuppression is possible if VALSTAR is inadvertently administered systemically or if significant systemic exposure occurs following intravesical administration (e.g., in patients with bladder rupture/perforation). Under such inadvertent exposures in the peritoneal cavity, the expected toxicities include leukopenia and neutropenia, beginning within 1 week of dose administration, with nadirs by the second week, and recovery generally by the third week. If VALSTAR is administered when bladder rupture or perforation is suspected, weekly monitoring of complete blood counts should be performed for 3 weeks.

11 DESCRIPTION

VALSTAR contains valrubicin (N-trifluoroacetyladriamycin-14-valerate), which is a semisynthetic analog of the anthracycline doxorubicin as a cytotoxic agent. The chemical name of valrubicin is (2 S- cis)-2-[1,2,3,4,6,11-hexahydro-2,5,12-trihydroxy-7-methoxy-6,11-dioxo-4-[[2,3,6-trideoxy-3-[(trifluoroacetyl)amino]-α-L- lyxo-hexopyranosyl]oxyl]-2-naphthacenyl]-2-oxoethylpentanoate. Valrubicin is an orange or orange-red powder that is highly lipophilic, soluble in methylene chloride, ethanol, methanol and acetone, and relatively insoluble in water. Its chemical formula is C34H36F3NO13and its molecular weight is 723.65. The chemical structure is shown in FIGURE 1.

VALSTAR is intended for intravesical administration in the urinary bladder. It is supplied as a nonaqueous solution that should be diluted before intravesical administration. Each vial of VALSTAR contains 200 mg valrubicin at a concentration of 40 mg/mL in 5 mL of 50% polyoxyl castor oil/50% dehydrated alcohol, USP without preservatives or other additives. The solution is sterile and nonpyrogenic.

12 CLINICAL PHARMACOLOGY

12.1 Mechanism of Action

Valrubicin is an anthracycline that affects a variety of interrelated biological functions, most of which involve nucleic acid metabolism. In cells, it inhibits the incorporation of nucleosides into nucleic acids, causes chromosomal damage, and arrests the cell cycle in G2. Although valrubicin does not bind strongly to DNA, valrubicin metabolites interfere with the normal DNA breaking-resealing action of DNA topoisomerase II.

12.3 Pharmacokinetics

When 800 mg VALSTAR was administered intravesically to patients with carcinoma in situ, VALSTAR penetrated into the bladder wall. The mean total anthracycline concentration measured in bladder tissue exceeded the levels causing 90% cytotoxicity to human bladder cells cultured in vitro. During the two-hour dose-retention period, the metabolism of VALSTAR to its major metabolites N-trifluoroacetyladriamycin and N-trifluoroacetyladriamycinol in bladder tissue was negligible. After retention, the drug was almost completely excreted by voiding the instillate. Mean percent recovery of VALSTAR, N-trifluoroacetyladriamycin, and total anthracyclines in 14 urine samples from six patients was 98.6%, 0.4%, and 99.0% of the total administered drug, respectively. During the two-hour dose-retention period, only nanogram quantities of VALSTAR were absorbed into the plasma. N-trifluoroacetyladriamycin and N-trifluoroacetyladriamycinol were measured in blood.

Total systemic exposure to anthracyclines during and after intravesical administration of VALSTAR is dependent upon the condition of the bladder wall. The mean AUC0-6hours(total anthracyclines exposure) for an intravesical dose of 900 mg of VALSTAR administered 2 weeks after transurethral resection of bladder tumors (n=6) was 78 nmol/L•hr. In patients receiving 800 mg of VALSTAR 5 to 51 minutes after typical (n=8) and extensive (n=5) TURB tumors, the mean AUC0-6hoursvalues for total anthracyclines were 409 and 788 nmol/L•hr, respectively. The AUC0-6hourstotal exposure to anthracyclines was 18,382 nmol/L•hr in one patient who experienced a perforated bladder following a transurethral resection that occurred 5 minutes before administration of an intravesical dose of 800 mg of VALSTAR. Administration of a comparable intravenous dose of VALSTAR (600 mg/m^2; n=2) as a 24-hour infusion resulted in an AUC0-6hoursfor total anthracyclines of 11,975 nmol/L•hr. These results are shown in FIGURE 2.

FIGURE 2.Comparison of Mean AUC0-6hours in VALSTAR Clinical Studies (N=number of patients)

13 NONCLINICAL TOXICOLOGY

13.1 Carcinogenesis, Mutagenesis, Impairment of Fertility

The carcinogenic potential of valrubicin has not been evaluated.

In vitro, valrubicin was mutagenic in the bacterial reverse mutation (Ames) assay and clastogenic in the chromosomal aberration assay in Chinese Hamster Ovary (CHO) cells.

Studies in animals evaluating the effects of valrubicin on male or female fertility have not been conducted. Based on effects on male reproductive organs in general toxicology studies in dogs with intravesical instillation, valrubicin may impair fertility in male patients. When instilled into the bladder of male dogs weekly for 6 weeks, valrubicin caused mild to moderate atrophy of the prostate with inflammation, diffuse decrease in acinar size, epithelial changes. It also caused testicular degeneration, marked germ cell depletion, spermatid giant cells and karyomegaly.

14 CLINICAL STUDIES

VALSTAR was administered intravesically to a total of 230 patients with transitional cell carcinoma of the bladder, including 205 patients who received multiple weekly doses ranging from 200 to 900 mg. One hundred seventy-nine of the 205 patients received the approved dose and schedule of 800 mg weekly for multiple weeks. Patients receiving VALSTAR for refractory carcinoma in situ were monitored for disease recurrence or progression with cystoscopy, biopsy, and urine cytology every 3 months.

In the 90 study patients with BCG-refractory carcinoma in situ(CIS), 70% had received at least 2 courses of BCG and 30% had received one course of BCG and at least one additional course of treatment with another agent(s) - e.g., mitomycin, thiotepa, or interferon. VALSTAR was administered beginning at least two weeks after transurethral resection and/or fulguration.

After intravesical administration of VALSTAR, 16 patients (18%) had a complete response documented by bladder biopsies and cytology at 6 months following initiation of therapy. Median duration of response from start of treatment varied according to the method of analysis (13.5 months if measured to last bladder biopsy without tumor and 21 months if measured until time of documented recurrence). A retrospective analysis in the 16 patients with complete response to VALSTAR demonstrated that time to recurrence of their disease after treatment with VALSTAR was longer than time to recurrence after previous courses of intravesical therapy.

Of the 90 patients with BCG-refractory CIS, 11% (10 patients) developed metastatic or deeply-invasive bladder cancer during follow-up; four of these patients, none who underwent cystectomy, died with metastatic bladder cancer and six were found to have developed stage progression to deeply-invasive disease (T3), with lymph node involvement in one patient, at the time of cystectomy. It is uncertain to what extent the development of advanced bladder cancer in these patients was due to the delay in cystectomy required to receive treatment with VALSTAR (3 months was the time of follow-up to determine response), as cystectomy was often delayed or was never performed despite failure of treatment with VALSTAR. In the 10 patients documented to have invasive bladder cancer or metastatic disease, the delay between the time of treatment failure (when cystectomy should have been performed) and cystectomy or documentation of advanced bladder cancer was a median of 17.5 months.

15 REFERENCES

1. OSHA Hazardous Drugs. OSHA. http://www.osha.gov/SLTC/hazardousdrugs/index.html.

16 HOW SUPPLIED/STORAGE AND HANDLING

VALSTAR is a sterile, clear red solution in polyoxyl castor oil/dehydrated alcohol, USP, containing 40 mg valrubicin per mL. VALSTAR is available in single-use, clear glass vials, individually packaged in the following sizes:

NDC 67979-001-01 Carton of four 200 mg/5 mL single-use vials

Store vials under refrigeration at 2°-8°C (36°-46°F) in the carton. DO NOT FREEZE.

17 PATIENT COUNSELING INFORMATION

Risk of Metastatic Bladder Cancer with Delayed Cystectomy

- Inform patients that VALSTAR has been shown to induce complete responses in only about 1 in 5 patients, and that delaying cystectomy could lead to development of metastatic bladder cancer, which is lethal. Discuss the relative risk of cystectomy versus the risk of metastatic bladder cancer [see Clinical Trials (14)] and that the risk increases the longer cystectomy is delayed in the presence of persisting CIS.

Local Adverse Reactions Before and During Treatment

- Inform patients that the major acute toxicities from VALSTAR are related to irritable bladder symptoms that may occur during instillation and retention of VALSTAR and for a limited period following voiding [see Adverse Reactions (6.1)] .
- Inform patients that for the first 24 hours following administration, red-tinged urine is typical.
- Advise patients to report prolonged irritable bladder symptoms or prolonged passage of red-colored urine immediately to their physician.
- Instruct patients to maintain adequate hydration following VALSTAR treatment.

Embryo-Fetal Toxicity

- Advise females of reproductive potential of the potential risk to a fetus and to use effective contraception during treatment with VALSTAR and for 6 months after the last dose. Advise females to inform their healthcare provider of a known or suspected pregnancy [see Warnings and Precautions (5.5), Use in Specific Populations (8.1and 8.3)] .
- Advise male patients with female partners of reproductive potential to use effective contraception during treatment with VALSTAR and for 3 months after the last dose [see Use in Specific Populations (8.3)] .

Lactation

- Advise females not to breastfeed during treatment with VALSTAR and for 2 weeks after the last dose [see Use in Specific Populations (8.2)] .

Healthcare professionals can telephone Endo (1-800-462-3636) for information on this product.

Manufactured for:
Endo USA
Malvern, PA 19355

Manufactured by:
BSP Pharmaceuticals S.p.A
Latina Scalo, Italy

© 2024 Endo, Inc. or one of its affiliates.

Revised: 07/2024